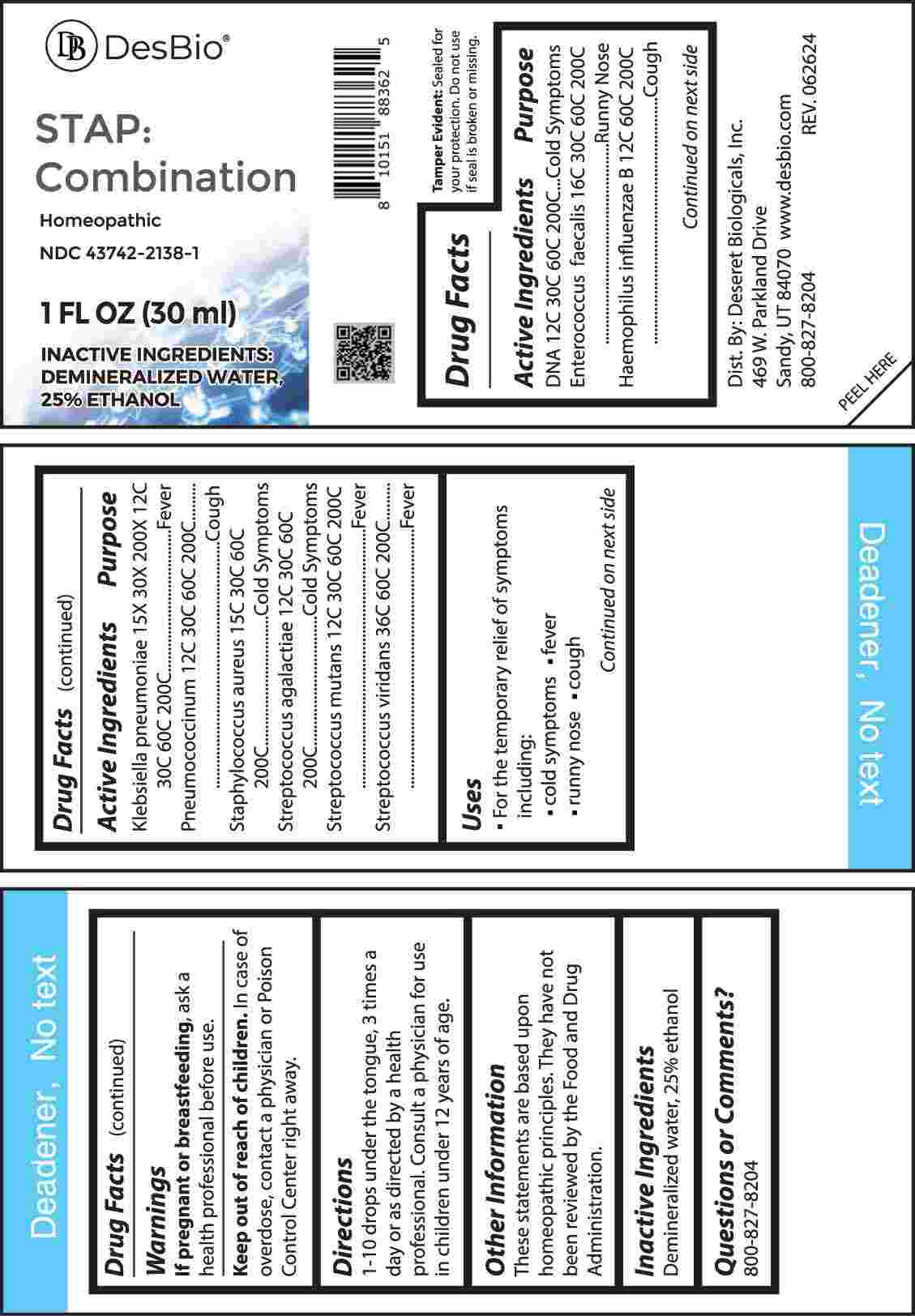 DRUG LABEL: Stap Combination
NDC: 43742-2138 | Form: LIQUID
Manufacturer: Deseret Biologicals, Inc.
Category: homeopathic | Type: HUMAN OTC DRUG LABEL
Date: 20241023

ACTIVE INGREDIENTS: HERRING SPERM DNA 12 [hp_C]/1 mL; ENTEROCOCCUS FAECALIS 16 [hp_C]/1 mL; HAEMOPHILUS INFLUENZAE TYPE B 12 [hp_C]/1 mL; KLEBSIELLA PNEUMONIAE 15 [hp_X]/1 mL; STREPTOCOCCUS PNEUMONIAE 12 [hp_C]/1 mL; STAPHYLOCOCCUS AUREUS 15 [hp_C]/1 mL; STREPTOCOCCUS AGALACTIAE 12 [hp_C]/1 mL; STREPTOCOCCUS MUTANS 12 [hp_C]/1 mL; STREPTOCOCCUS VIRIDANS GROUP 36 [hp_C]/1 mL
INACTIVE INGREDIENTS: WATER; ALCOHOL

DRUG FACTS:

ACTIVE INGREDIENTS:

DNA 12C, 30C, 60C, 200C, Enterococcus Faecalis 16C, 30C, 60C, 200C, Haemophilus Influenzae B 12C, 60C, 200C, Klebsiella Pneumoniae 15X, 30X, 200X, 12C, 30C, 60C, 200C, Pneumococcinum 12C, 30C, 60C, 200C, Staphylococcus Aureus 15C, 30C, 60C, 200C, Streptococcus Agalactiae 12C, 30C, 60C, 200C, Streptococcus Mutans 12C, 30C, 60C, 200C, Streptococcus Viridans 36C, 60C, 200C.

PURPOSE:

DNA – Cold Symptoms, Enterococcus Faecalis – Runny Nose, Haemophilus Influenzae B - Cough, Klebsiella Pneumoniae - Fever, Pneumococcinum - Cough, Staphylococcus Aureus – Cold Symptoms, Streptococcus Agalactiae – Cold Symptoms, Streptococcus Mutans - Fever, Streptococcus Viridans- Fever

USES:

• For the temporary relief of symptoms including:

• cold symptoms • fever • runny nose • cough

These statements are based upon homeopathic principles. They have not been reviewed by the Food and Drug Administration.

WARNINGS:

If pregnant or breast-feeding, ask a health professional before use.

Keep out of reach of children. In case of overdose, contact a physician or Poison Control Center right away.

Tamper Evident: Sealed for your protection. Do not use if seal is broken or missing.

KEEP OUT OF REACH OF CHILDREN:

In case of overdose, contact a physician or Poison Control Center right away.

DIRECTIONS:

1-10 drops under the tongue, 3 times a day or as directed by a health professional. Consult a physician for use in children under 12 years of age.

INACTIVE INGREDIENTS:

Demineralized water, 25% ethanol

QUESTIONS:

Dist. By: Deseret Biologicals, Inc.
469 W. Parkland Drive
Sandy, UT 84070

www.desbio.com

800-827-8204

PACKAGE LABEL DISPLAY:

DesBio

STAP:Combination

Homeopathic

NDC 43742-2138-1

1 FL OZ (30 ml)